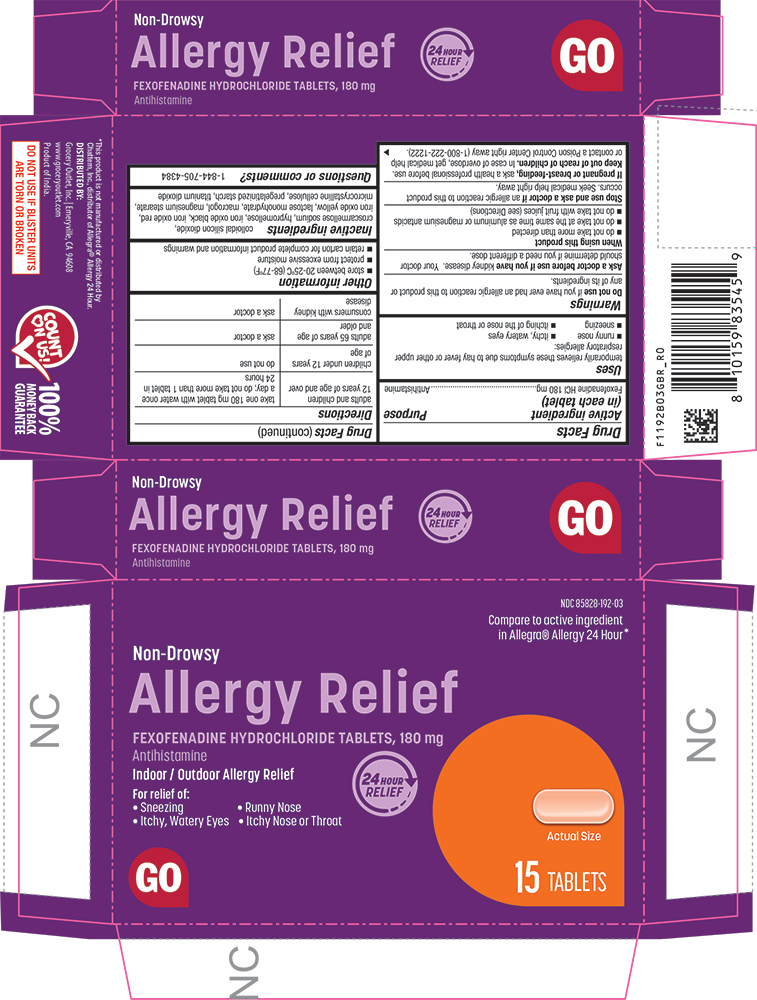 DRUG LABEL: Allergy Relief
NDC: 85828-192 | Form: TABLET
Manufacturer: Grocery Outlet, Inc.
Category: otc | Type: HUMAN OTC DRUG LABEL
Date: 20260218

ACTIVE INGREDIENTS: FEXOFENADINE HYDROCHLORIDE 180 mg/1 1
INACTIVE INGREDIENTS: CROSCARMELLOSE SODIUM; FERROSOFERRIC OXIDE; FERRIC OXIDE RED; FERRIC OXIDE YELLOW; HYPROMELLOSE 2910 (15 MPA.S); LACTOSE MONOHYDRATE; MAGNESIUM STEARATE; MICROCRYSTALLINE CELLULOSE; POLYETHYLENE GLYCOL 6000; SILICON DIOXIDE; STARCH, CORN; TITANIUM DIOXIDE

1192B-GBR-2026-0218

Drug Facts

Active ingredient (in each tablet)

Fexofenadine HCl 180 mg

Purpose

Antihistamine

Uses

temporarily relieves these symptoms due to hay fever or other upper respiratory allergies:

- runny nose
- sneezing
- itchy, watery eyes
- itching of the nose or throat

Warnings

Do not use if you have ever had an allergic reaction to this product or any of its ingredients.

Ask a doctor before use if you havekidney disease. Your doctor should determine if you need a different dose.

When using this product

- do not take more than directed
- do not take at the same time as aluminum or magnesium antacids
- do not take with fruit juices (see Directions)

Stop use and ask a doctor ifan allergic reaction to this product occurs. Seek medical help right away.

PREGNANCY OR BREAST FEEDING

If pregnant or breast-feeding, ask a health professional before use.

Keep out of reach of children.In case of overdose, get medical help or contact a Poison Control Center right away (1-800-222-1222).

Directions

adults and children 12 years of age and over | take one 180 mg tablet with water once a day; do not take more than 1 tablet in 24 hours
children under 12 years of age | do not use
adults 65 years of age and older | ask a doctor
consumers with kidney disease | ask a doctor

Other information

- store between 20-25°C (68-77°F)
- protect from excessive moisture
- retain carton for complete product information and warnings

Inactive ingredients

colloidal silicon dioxide, croscarmellose sodium, hypromellose, iron oxide black, iron oxide red, iron oxide yellow, lactose monohydrate, macrogol, magnesium stearate, microcrystalline cellulose, pregelatinized starch, titanium dioxide

Questions or comments?

1-844-705-4384

PRINCIPAL DISPLAY PANEL

NDC 85828-192-03

Compare to active ingredient in Allergra® Allergy 24 Hour*

Non-Drowsy

Allergy Relief

FEXOFENADINE HYDROCHLORIDE TABLETS, 180 mg

Antihistamine

Indoor / Outdoor Allergy Relief

24 HOUR RELIEF

For Relief of:

• Sneezing

• Runny Nose

• Itchy, Watery Eyes

• Itchy Nose or Throat

GO

Actual Size

15 TABLETS